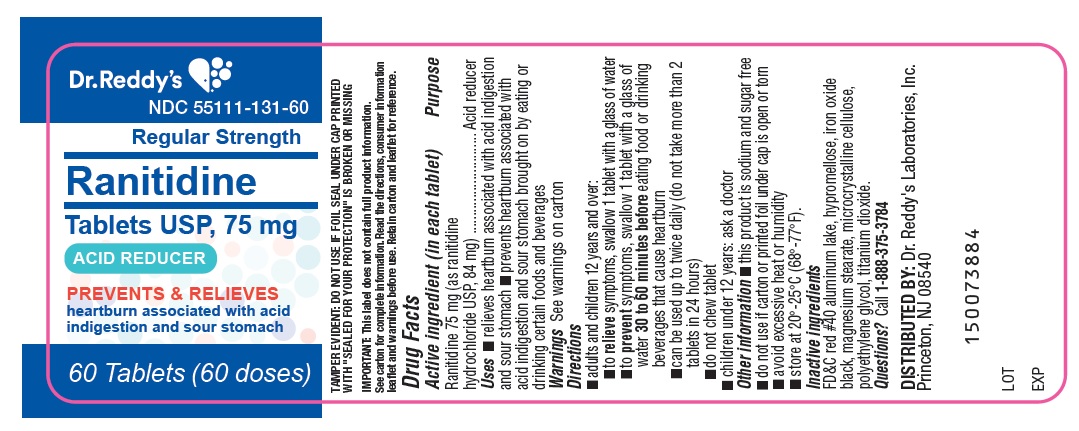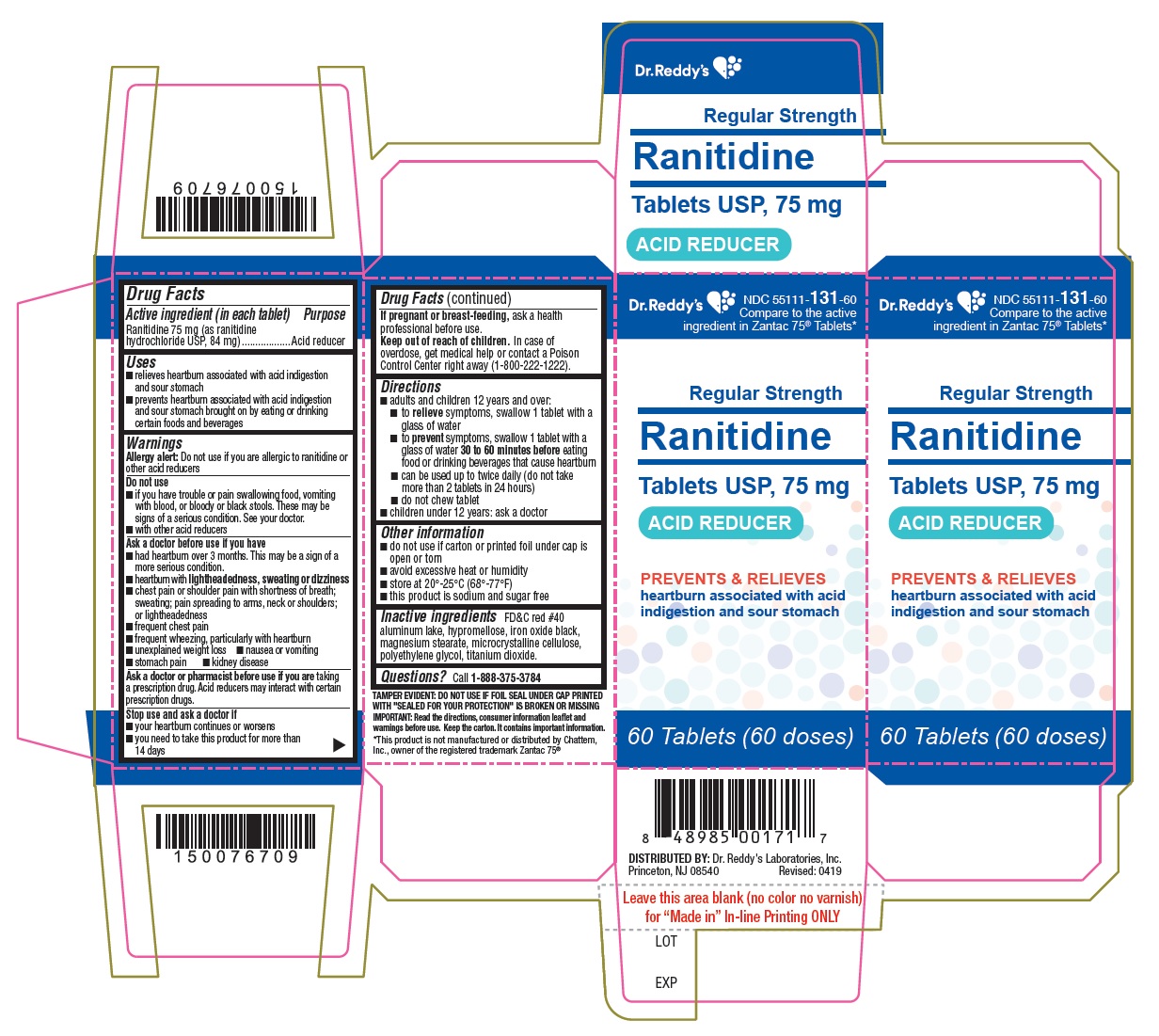 DRUG LABEL: Ranitidine
NDC: 55111-131 | Form: TABLET
Manufacturer: Dr. Reddy's Laboratories Limited
Category: otc | Type: HUMAN OTC DRUG LABEL
Date: 20250523

ACTIVE INGREDIENTS: ranitidine hydrochloride 75 mg/1 1
INACTIVE INGREDIENTS: HYPROMELLOSES; magnesium stearate; cellulose, microcrystalline; Polyethylene Glycol, Unspecified; ferrosoferric oxide; titanium dioxide

Drug Facts

Active ingredient (in each tablet)

Ranitidine 75 mg (as ranitidine hydrochloride, USP 84 mg)

Purpose

Acid reducer

Uses

- relieves heartburn associated with acid indigestion and sour stomach
- prevents heartburn associated with acid indigestion and sour stomach brought on by eating or drinking certain foods and beverages

Warnings

Allergy alert: Do not use if you are allergic to ranitidine or other acid reducers

Do not use

- if you have trouble or pain swallowing food, vomiting with blood, or bloody or black stools.
  These may be signs of a serious condition. See your doctor.
- with other acid reducers

Ask a doctor before use if you have

- had heartburn over 3 months. This may be a sign of a more serious condition.
- heartburn with lightheadedness, sweating or dizziness
- chest pain or shoulder pain with shortness of breath; sweating; pain spreading to arms, neck or shoulders; or lightheadedness
- frequent chest pain
- frequent wheezing, particularly with heartburn
- unexplained weight loss
- nausea or vomiting
- stomach pain
- kidney disease

Ask a doctor or pharmacist before use if you are

• taking a prescription drug. Acid reducers may interact with certain prescription drugs.

Stop use and ask a doctor if

- your heartburn continues or worsens
- you need to take this product for more than 14 days

PREGNANCY OR BREAST FEEDING

If pregnant or breast-feeding, ask a health professional before use.

Keep out of reach of children.In case of overdose, get medical help or contact a Poison Control Center right away (1-800-222-1222).

Directions

- adults and children 12 years and over:
  - to relieve symptoms, swallow 1 tablet with a glass of water
  - to prevent symptoms, swallow 1 tablet with a glass of water 30 to 60 minutes before eating food or drinking beverages that cause heartburn
  - can be used up to twice daily (do not take more than 2 tablets in 24 hours)
  - do not chew tablet
- children under 12 years: ask a doctor

Other information

- this product is sodium and sugar free
- Blister: do not use if individual blister unit is open or torn
  Bottle: do not use if printed foil under bottle cap is open or torn
- avoid excessive heat or humidity
- store at 20°-25°C (68°-77°F)

Inactive ingredients

FD&C red #40 aluminum lake, hypromellose, iron oxide black, magnesium stearate, microcrystalline cellulose, polyethylene glycol, titanium dioxide.

Questions? call 1-888-375-3784

Read the directions, consumer information leaflet and warnings before use. Keep the carton. It contains important information.

Ranitidine Tablets USP, 75 mg - container label

PACKAGE LABEL

Ranitidine Tablets USP, 75 mg - Container CartonLabel